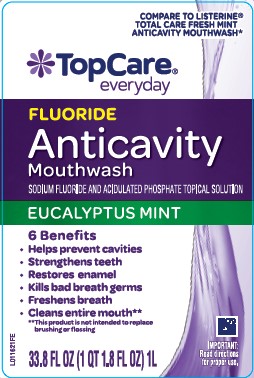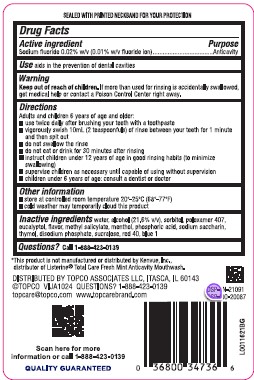 DRUG LABEL: Mouth Rinse
NDC: 36800-001 | Form: MOUTHWASH
Manufacturer: Topco Associates LLC
Category: otc | Type: HUMAN OTC DRUG LABEL
Date: 20260213

ACTIVE INGREDIENTS: SODIUM FLUORIDE 0.1 mg/1 mL
INACTIVE INGREDIENTS: WATER; ALCOHOL; SORBITOL; POLOXAMER 407; EUCALYPTOL; METHYL SALICYLATE; MENTHOL; PHOSPHORIC ACID; SACCHARIN SODIUM; THYMOL; SODIUM PHOSPHATE, DIBASIC, ANHYDROUS; SUCRALOSE; FD&C RED NO. 40; FD&C BLUE NO. 1

Top Care 163.005/163AG
Anticavity Fluoride Rinse

Tamper Evident Statement

SEALED WITH PRINTED NECKBAND FOR YOUR PROTECTION

Active ingredient

Sodium fluoride 0.02% (0.01% w/v fluoride ion)

Purpose

Anticavity

Use

aids in the prevention of dental cavities

Warnings

for this product

Keep out of reach of children.

If more than used for rinsing is accidentally swallowed, get medical help or contact a Poison Control Center right away.

Directions

Adults and children under 12 years of age and older:

•use twice daily after brushing your teeth with a toothpaste

•vigorously swish 10 mL (2 teaspoonfuls) of rinse between your teeth for 1 minute and then spit out

•do not swallow the rinse

•do not eat or drink anything for 30 minutes after rinsing

•instruct children under 12 years of age in good rinsing habits (to minimize swallowing)

•supervise children as necessary until capable of using without supervision

•children under 12 years of age: consult a dentist or doctor

Other information

•store at controlled room temperature 20⁰ - 25⁰C (68⁰ - 77⁰ F)

•cold weather may temporarily cloud this product

Inactive ingredients

water, alcohol (21.6 %v/v), sorbitol, poloxamer 407, eucalyptol, flavor, methyl salicylate, menthol, phosphoric acid, sodium saccharin, thymol, disodium phosphate, sucralose, red 40, blue 1

Disclaimer

*This product is not manufactured or distributed by Kenvue, Inc., distributor of Listerine®Total Care Fresh Mint Anticavity Mouthwash.

ADVERSE REACTION

DISTRIBUTED BY TOPCO ASSOCIATES LLC, ITASCA, IL 60143

TOPCO VIJA0219 QUESTIONS? 1-888-423-0139 topcare@topco.com

TOPCO VIJA1024 QUESTIONS? 1-888-423-0139

topcare@topco.com www.topcarebrand.com

DSP-TN-21091

DSP-MO-20087

Scan her for more information or call 1-888-423-0139

QUALITY GUARANTEED

PRINCIPAL DISPLAY PANEL

COMPARE TO LISTERINE®TOTAL CARE FRESH MINT ANTICAVITY MOUTHWASH*

TopCare®

everyday

FLUORIDE

Anticavity

Mouthwash

SODIUM FLUORIDE AND ACIDULATED PHOSPHATE TOPICAL SOLUTION

EUCALYPTUS MINT

6 Benefits

- Helps prevent cavities
- Strengthens teeth
- Restores enamel
- Kills bad breath germs
- Freshens breath
- Cleans entire mouth**

**This product is not intended to replace brushing or flossing

IMPORTANT: Read directions for proper use.

33.8 FL OZ (1 QT 1.8 FL OZ) 1 L